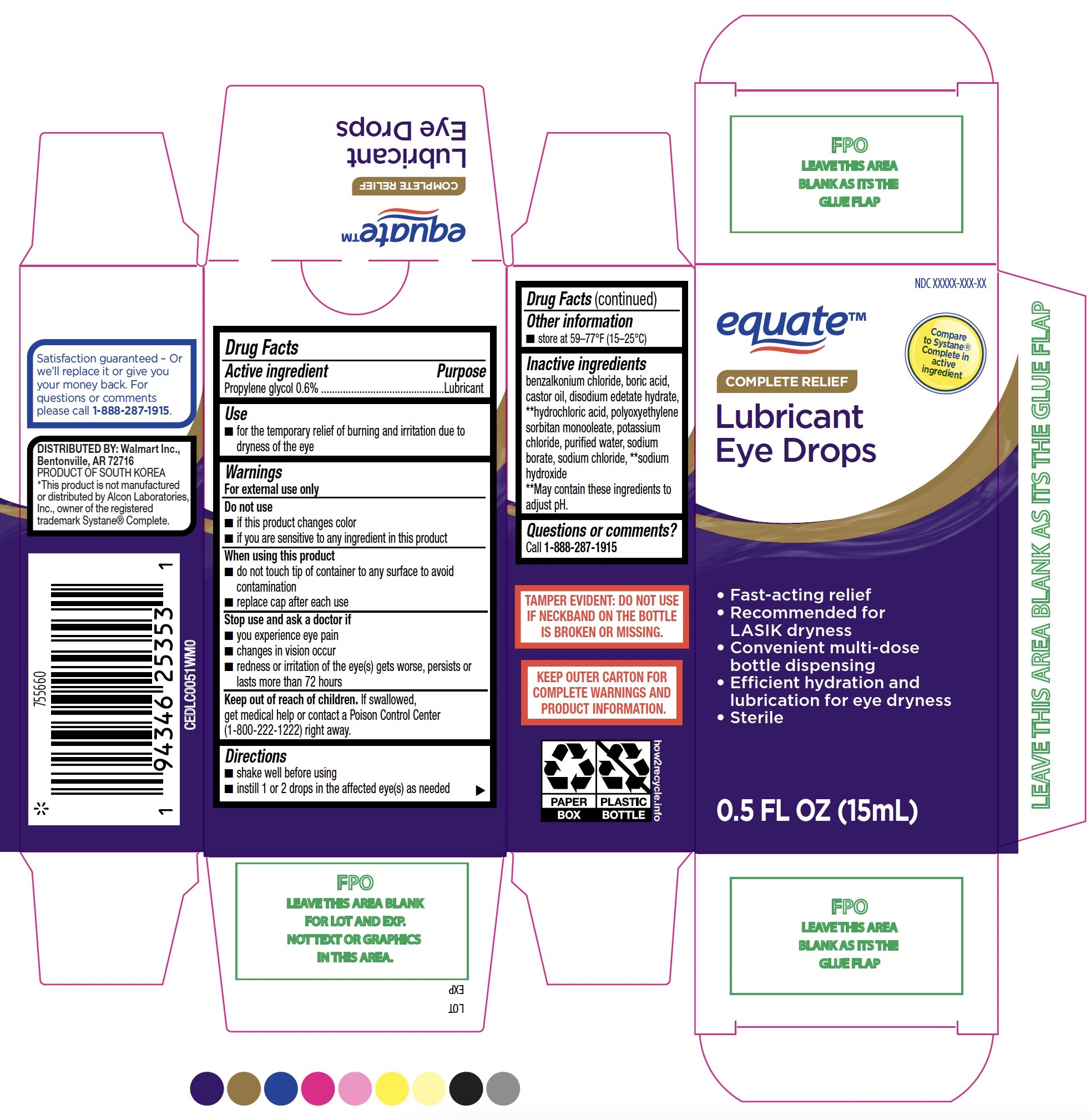 DRUG LABEL: Equate Complete Relief Lubricant Eye Drops
NDC: 79903-259 | Form: SOLUTION/ DROPS
Manufacturer: Walmart Inc.
Category: otc | Type: HUMAN OTC DRUG LABEL
Date: 20251230

ACTIVE INGREDIENTS: PROPYLENE GLYCOL 0.6 g/100 mL
INACTIVE INGREDIENTS: POTASSIUM CHLORIDE; WATER; SODIUM BORATE; BORIC ACID; CASTOR OIL; PEG-6 SORBITAN OLEATE; BENZALKONIUM CHLORIDE; EDETATE DISODIUM; SODIUM CHLORIDE; SODIUM HYDROXIDE; HYDROCHLORIC ACID

Equate Complete Relief Lubricant Eye Drops 15mL (PLD)

Active ingredient

Propylene glycol 0.6%

Purpose

Lubricant

Use

- for the temporary relief of burning and irritation due to dryness of the eye

Warnings

For external use only

Do not use

- if this product changes color
- if you are sensitive to any ingredient in this product

When using this product

- do not touch tip of container to any surface to avoid contamination
- repace cap after each use

Stop use and ask a doctor if

- you experience eye pain
- changes in vision occur
- redness or irritation of the eye(s) gets worse, persists or lasts more than 72 hours

Keep out of reach of children.

If swallowed, get medical help or contact a Poison Control Center (1-800-222-1222) right away.

Directions

- shake well before using
- instill 1 or 2 drops in the affected eye(s) as needed

Other information

- store at 59-77°F (15-25°C)

Inactive ingredients

benzalkonium chloride, boric acid, castor oil, disodium edetate hydrate, **hydrochloric acid, polyoxyethylene sorbitan monooleate, potassium chloride, purified water, sodium borate, sodium chloride, **sodium hydroxide

**May contain these ingredients to adjust pH.

Questions or comments?

Call 1-888-287-1915